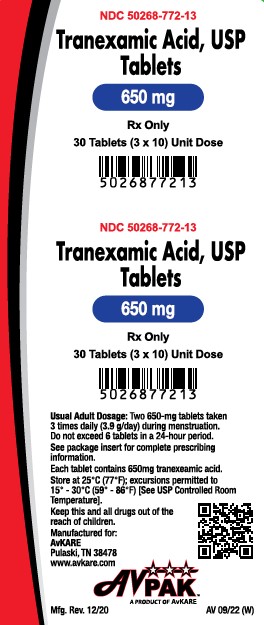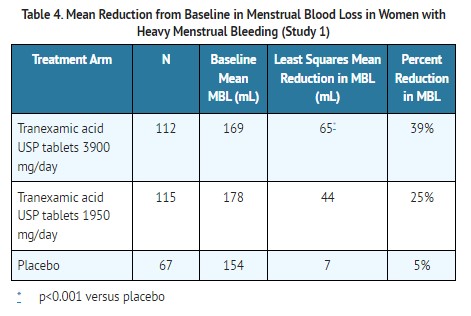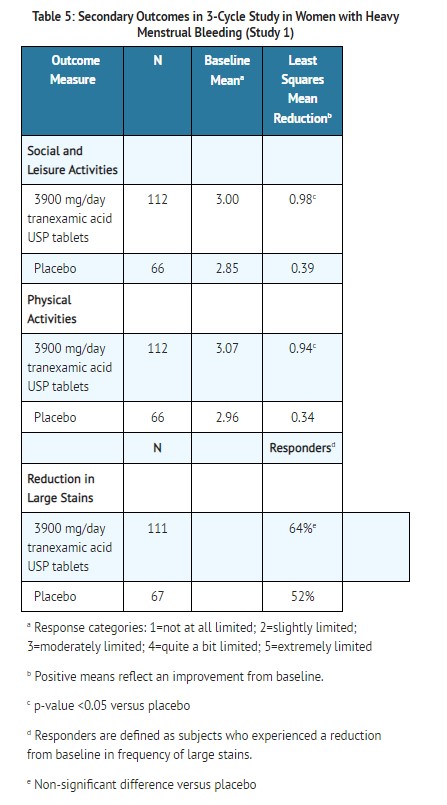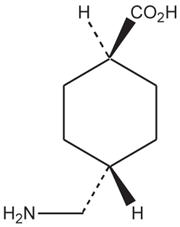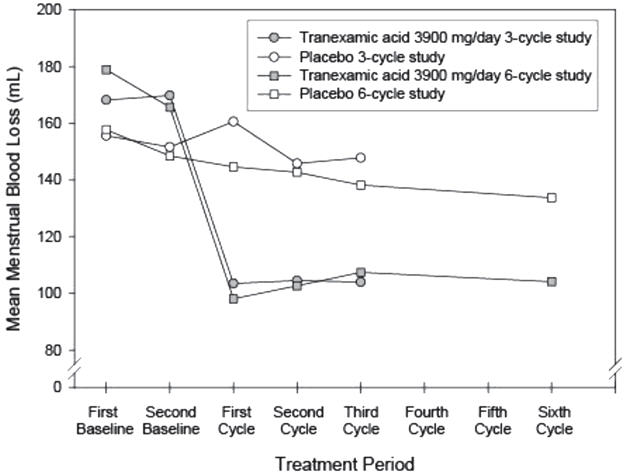 DRUG LABEL: Tranexamic Acid
NDC: 50268-772 | Form: TABLET
Manufacturer: AvPAK
Category: prescription | Type: HUMAN PRESCRIPTION DRUG LABEL
Date: 20260112

ACTIVE INGREDIENTS: TRANEXAMIC ACID 650 mg/1 1
INACTIVE INGREDIENTS: SILICON DIOXIDE; MICROCRYSTALLINE CELLULOSE; STARCH, CORN; POVIDONE, UNSPECIFIED; HYPROMELLOSE, UNSPECIFIED; STEARIC ACID; MAGNESIUM STEARATE

HIGHLIGHTS OF PRESCRIBING INFORMATION

Tranexamic Acid Tablet, USP
Rx Only
These highlights do not include all the information needed to use TRANEXAMIC ACID USP TABLETS safely and effectively. See full prescribing information for TRANEXAMIC ACID USP TABLETS.
Initial U.S. Approval: 1986

1 INDICATIONS AND USAGE

Tranexamic acid USP tablets is an antifibrinolytic indicated for the treatment of cyclic heavy menstrual bleeding in females of reproductive potential. (1)

2 DOSAGE AND ADMINISTRATION

- 1,300 mg three times a day (3,900 mg/day) for a maximum of 5 days during monthly menstruation (2.1)
- Renal impairment: Lower dosage is needed (for a maximum of 5 days during menstruation) if serum creatinine concentration (Cr) is higher than 1.4 mg/dL (2.2)
  - Cr above 1.4 mg/dL and ≤ 2.8 mg/dL: 1,300 mg two times a day (2,600 mg/day)
  - Cr above 2.8 mg/dL and ≤ 5.7 mg/dL: 1,300 mg once a day (1,300 mg/day)
  - Cr above 5.7 mg/dL: 650 mg once a day (650 mg/day)

3 DOSAGE FORMS AND STRENGTHS

Tablets: 650 mg (3)

4 CONTRAINDICATIONS

- Concomitant use of combined hormonal contraceptives (4.1)
- Active thromboembolic disease or a history or intrinsic risk of thrombosis or thromboembolism, including retinal vein or artery occlusion (4.1)
- Hypersensitivity to tranexamic acid (4.2)

5 WARNINGS AND PRECAUTIONS

- Thromboembolism, including retinal occlusion, has been reported with tranexamic acid USP tablets use. Concomitant use of tranexamic acid USP tablets with combined hormonal contraceptives, Factor IX complex concentrates, anti-inhibitor coagulant concentrates or all-trans retinoic acid (oral tretinoin) may increase the risk of thrombosis. (5.1)
- Visual or ocular adverse reactions may occur with tranexamic acid USP tablets. Immediately discontinue use if visual or ocular symptoms occur. (5.1)
- In case of severe allergic reaction, discontinue tranexamic acid USP tablets and seek immediate medical attention. (5.2)
- Cerebral edema and cerebral infarction may be caused by use of tranexamic acid USP tablets in patients with subarachnoid hemorrhage. (5.3)
- Ligneous conjunctivitis has been reported in patients taking tranexamic acid. (5.4)

6 ADVERSE REACTIONS

Most common adverse reactions in clinical trials (≥ 5%, and more frequent in tranexamic acid USP tablets-treated subjects compared to placebo-treated subjects) are headache, sinus and nasal symptoms, back pain, abdominal pain, musculoskeletal pain, joint pain, muscle cramps, migraine, anemia and fatigue. (6.1)

To report SUSPECTED ADVERSE REACTIONS, contact AvKARE at 1-855-361-3993 or FDA at 1-800-FDA-1088 or www.fda.gov/medwatch.

7 DRUG INTERACTIONS

Concomitant therapy with tissue plasminogen activators may decrease the efficacy of both tranexamic acid USP tablets and tissue plasminogen activators. (7.2)

8 USE IN SPECIFIC POPULATIONS

- Geriatric use: Tranexamic acid USP tablets is not indicated for use in postmenopausal women (8.5)
- Renal impairment: A lower dosage is needed. (2.2, 8.6)
- Hepatic impairment: No dosage adjustment is needed. (8.7)

FULL PRESCRIBING INFORMATION

1 INDICATIONS AND USAGE

Tranexamic acid USP tablets are indicated for the treatment of cyclic heavy menstrual bleeding in females of reproductive potential [see Clinical Studies (14)].

2 DOSAGE AND ADMINISTRATION

2.1 Recommended Testing Prior to Tranexamic Acid USP Tablets Administration

Prior to prescribing tranexamic acid USP tablets, exclude endometrial pathology that can be associated with heavy menstrual bleeding.

2.2 Recommended Dosage

The recommended dosage of tranexamic acid USP tablets for patients with normal renal function is 1300 mg orally three times daily (3900 mg/day) for a maximum of 5 days during monthly menstruation. Tranexamic acid USP tablets may be administered with or without food. Swallow tablets whole; do not chew or break apart.

2.3 Dosage Recommendations in Patients with Renal Impairment

The recommended dosage (for a maximum of 5 days during monthly menstruation) in patients with renal impairment with serum creatinine concentration higher than 1.4 mg/dL is described in Table 1.

Table 1. Recommended Dosage of Tranexamic Acid USP Tablets in Patients with Renal Impairment
Serum Creatinine (mg/dL) | Recommended Dosage (maximum of 5 days during menstruation) | Total Daily Dose
Above 1.4 and ≤ 2.8 | 1300 mg two times a day | 2600 mg
Above 2.8 and ≤ 5.7 | 1300 mg once a day | 1300 mg
Above 5.7 | 650 mg once a day | 650 mg

3 DOSAGE FORMS AND STRENGTHS

Tablets: 650 mg white oval-shaped debossed with the marking “FP650”

4 CONTRAINDICATIONS

4.1 Thromboembolic Risk

Tranexamic acid USP tablets are contraindicated in females of reproductive potential who are [see Warnings and Precautions (5.1)]:

- Using combined hormonal contraception
- Known to have any of the following conditions:
  - Active thromboembolic disease (e.g., deep vein thrombosis, pulmonary embolism, or cerebral thrombosis)
  - A history of thrombosis or thromboembolism, including retinal vein or artery occlusion
  - An intrinsic risk of thrombosis or thromboembolism (e.g., thrombogenic valvular disease, thrombogenic cardiac rhythm disease, or hypercoagulopathy)

4.2 Hypersensitivity to Tranexamic Acid

Tranexamic acid USP tablets are contraindicated in females with reproductive potential with known hypersensitivity to tranexamic acid [see Warnings and Precautions (5.2) and Adverse Reactions (6.1)] .

5 WARNINGS AND PRECAUTIONS

5.1 Thromboembolic Risk

Venous and arterial thrombosis or thromboembolism, as well as cases of retinal artery and retinal vein occlusions, have been reported with tranexamic acid USP tablets.

Retinal venous and arterial occlusion have been reported in patients using tranexamic acid. Patients should be instructed to report visual and ocular symptoms promptly. In the event of such symptoms, patients should be instructed to discontinue tranexamic acid USP tablets immediately and should be referred to an ophthalmologist for a complete ophthalmic evaluation, including dilated retinal examination, to exclude the possibility of retinal venous or arterial occlusion.

Concomitant Use of Hormonal Contraceptives

Combined hormonal contraceptives are known to increase the risk of venous thromboembolism, as well as arterial thromboses such as stroke and myocardial infarction. Because tranexamic acid USP tablets are antifibrinolytic, the risk of venous thromboembolism, as well as arterial thromboses such as stroke, may increase further when combined hormonal contraceptives are administered with tranexamic acid USP tablets. This is of particular concern in women who are obese or smoke cigarettes, especially smokers over 35 years of age.

Women using combined hormonal contraception were excluded from the clinical trials supporting the safety and efficacy of tranexamic acid USP tablets, and there are no clinical trial data on the risk of thrombotic events with the concomitant use of tranexamic acid USP tablets with combined hormonal contraceptives. However, there have been US postmarketing reports of venous and arterial thrombotic events in women who have used tranexamic acid USP tablets concomitantly with combined hormonal contraceptives. For this reason, concomitant use of tranexamic acid with combined hormonal contraceptives is contraindicated [see Contraindications (4.1) and Drug Interactions (7.1)].

Concomitant Use with Factor IX Complex Concentrates or Anti-Inhibitor Coagulant Concentrates

Tranexamic acid USP tablets are not recommended in patients taking either Factor IX complex concentrates or anti-inhibitor coagulant concentrates because the risk of thrombosis may be increased [see Drug Interactions (7.3) and Clinical Pharmacology (12.3)].

Patients with Acute Promyelocytic Leukemia Taking Concomitant All-Trans Retinoic Acid (Oral Tretinoin)

Tranexamic acid USP tablets are not recommended in patients with acute promyelocytic leukemia taking all-trans retinoic acid for remission induction because of possible exacerbation of the procoagulant effect of all-trans retinoic acid [see Drug Interactions (7.4) and Clinical Pharmacology (12.3)].

5.2 Severe Allergic Reactions

A case of severe allergic reaction to tranexamic acid USP tablets was reported in the clinical trials, involving a subject who experienced dyspnea, tightening of her throat, and facial flushing that required emergency medical treatment. A case of anaphylactic shock has also been reported in the literature, involving a patient who received an intravenous bolus of tranexamic acid. Tranexamic acid USP tablets are contraindicated in females of reproductive potential with known hypersensitivity to tranexamic acid.

5.3 Subarachnoid Hemorrhage

Cerebral edema and cerebral infarction may be caused by use of tranexamic acid USP tablets in patients with subarachnoid hemorrhage.

5.4 Ligneous Conjunctivitis

Ligneous conjunctivitis has been reported in patients taking tranexamic acid. The conjunctivitis resolved following cessation of tranexamic acid USP tablets.

6 ADVERSE REACTIONS

6.1 Clinical Trial Experience

Because clinical trials are conducted under widely varying conditions, adverse reaction rates observed in the clinical trials of a drug cannot be directly compared to the rates in the clinical trials of another drug and may not reflect the rates observed in clinical practice.

Adverse Reactions in Short-term Studies

The safety of tranexamic acid USP tablets in the treatment of heavy menstrual bleeding in females of reproductive potential was studied in two randomized, double-blind, placebo-controlled studies [see Clinical Studies (14)].

- Study 1 compared the effects of two doses of tranexamic acid USP tablets (1950 mg and 3900 mg per day for up to 5 days during each menstrual period) versus placebo over a 3-cycle treatment duration. A total of 304 women were randomized to this study, with 115 receiving at least one dose of 3900 mg/day of tranexamic acid USP tablets.
- Study 2 compared the effects of tranexamic acid USP tablets (3900 mg/day) versus placebo over a 6-cycle treatment duration. A total of 196 women were randomized to this study, with 117 receiving at least one dose of tranexamic acid USP tablets.

Across the studies, the combined exposure to 3900 mg/day tranexamic acid USP tablets was 947 cycles and the average duration of use was 3.4 days per cycle. In both studies, subjects were generally healthy women who had menstrual blood loss of ≥ 80 mL. In these studies, subjects were 18 to 49 years of age with a mean age of approximately 40 years, had cyclic menses every 21-35 days, and a body mass index (BMI) of approximately 32 kg/m^2. On average, subjects had a history of heavy menstrual bleeding for approximately 10 years and 40% had fibroids as determined by transvaginal ultrasound. Approximately 70% were Caucasian, 25% were Black, and 5% were Asian, Native American, Pacific Islander, or Other. Seven percent (7%) of all subjects were of Hispanic origin. Women using hormonal contraception were excluded from the trials.

A list of adverse reactions occurring in ≥ 5% of subjects and more frequently in tranexamic acid USP tablets-treated subjects receiving 3900 mg/day compared to placebo-treated subjects is provided in Table 2.

Table 2. Adverse Reactions* Reported in Women with Heavy Menstrual Bleeding (Studies 1 and 2)
 | Tranexamic acid USP tablets 3900 mg/day n (%) (N=232) | Placebo n (%) (N=139)
Number of Subjects with at Least One Adverse Reaction | 208 (89.7%) | 122 (87.8%)
Headachea | 117 (50.4%) | 65 (46.8%)
Nasal & sinus symptomsb | 59 (25.4%) | 24 (17.3%)
Back pain | 48 (20.7%) | 21 (15.1%)
Abdominal painc | 46 (19.8%) | 25 (18.0%)
Musculoskeletal paind | 26 (11.2%) | 4 (2.9%)
Arthralgiae | 16 (6.9%) | 7 (5.0%)
Muscle cramps & spasms | 15 (6.5%) | 8 (5.8%)
Migraine | 14 (6.0%) | 8 (5.8%)
Anemia | 13 (5.6%) | 5 (3.6%)
Fatigue | 12 (5.2%) | 6 (4.3%)
* Adverse reactions that were reported by ≥ 5% of tranexamic acid USP tablets-treated subjects and more frequently in tranexamic acid USP tablets -treated subjects compared to placebo-treated subjects
a Includes headache and tension headache
b Nasal and sinus symptoms include nasal, respiratory tract and sinus congestion, sinusitis, acute sinusitis, sinus headache, allergic sinusitis and sinus pain, and multiple allergies and seasonal allergies
c Abdominal pain includes abdominal tenderness and discomfort
d Musculoskeletal pain includes musculoskeletal discomfort and myalgia
e Arthralgia includes joint stiffness and swelling

Adverse Reactions in Long-term Studies

Long-term safety of tranexamic acid USP tablets was studied in two open-label studies. In one study, subjects with physician-diagnosed heavy menstrual bleeding (not using the alkaline hematin methodology) were treated with 3900 mg/day for up to 5 days during each menstrual period for up to 27 menstrual cycles. A total of 781 subjects were enrolled and 239 completed the study through 27 menstrual cycles. A total of 12.4% of the subjects withdrew due to adverse reactions. Women using hormonal contraception were excluded from the study. The total exposure in this study to 3900 mg/day tranexamic acid USP tablets was 10,213 cycles. The average duration of tranexamic acid USP tablets use was 2.9 days per cycle.

A long-term open-label extension study of subjects from the two short-term efficacy studies was also conducted in which subjects were treated with 3900 mg/day for up to 5 days during each menstrual period for up to 9 menstrual cycles. A total of 288 subjects were enrolled and 196 subjects completed the study through 9 menstrual cycles. A total of 2.1% of the subjects withdrew due to adverse reactions. The total exposure to 3900 mg/day tranexamic acid USP tablets in this study was 1,956 cycles. The average duration of tranexamic acid USP tablets use was 3.5 days per cycle.

The types and severity of adverse reactions in these two long-term open-label trials were similar to those observed in the double-blind, placebo-controlled studies although the percentage of subjects reporting them was greater in the 27-month study, most likely because of the longer study duration.

A case of severe allergic reaction to tranexamic acid USP tablets was reported in the extension trial, involving a subject on her fourth cycle of treatment, who experienced dyspnea, tightening of her throat, and facial flushing that required emergency medical treatment.

6.2 Postmarketing Experience

The following adverse reactions have been identified from postmarketing experience with tranexamic acid USP tablets. Because these reactions are reported voluntarily from a population of uncertain size, it is not always possible to reliably estimate their frequency or establish a causal relationship to drug exposure.

- Eye disorders: Impaired color vision and other visual disturbances
- Gastrointestinal disorders: Nausea, vomiting, and diarrhea
- Immune system disorders: Anaphylactic shock and anaphylactoid reactions
- Nervous system disorders: Dizziness
- Skin and subcutaneous tissue disorders: Allergic skin reactions
- Vascular disorders: Thromboembolic events (e.g., deep vein thrombosis, pulmonary embolism, cerebral thrombosis, acute renal cortical necrosis, and central retinal artery and vein obstruction); cases have been associated with concomitant use of combined hormonal contraceptives

7 DRUG INTERACTIONS

No drug-drug interaction studies were conducted with tranexamic acid USP tablets.

7.1 Combined Hormonal Contraceptives

Because tranexamic acid USP tablets are antifibrinolytic, concomitant use of combined hormonal contraception and tranexamic acid USP tablets may increase the thrombotic risk associated with combined hormonal contraceptives. For this reason, concomitant use of tranexamic acid USP tablets with combined hormonal contraceptives is contraindicated [see Contraindications (4) and Warnings and Precautions (5.1)].

7.2 Tissue Plasminogen Activators

Concomitant therapy with tissue plasminogen activators may decrease the efficacy of both tranexamic acid USP tablets and tissue plasminogen activators. Discontinue tranexamic acid USP tablets if a patient requires tissue plasminogen activators.

7.3 Factor IX Complex Concentrates or Anti-Inhibitor Coagulant Concentrates

Tranexamic acid USP tablets are not recommended in patients taking either Factor IX complex concentrates or anti-inhibitor coagulant concentrates because the risk of thrombosis may be increased [see Warnings and Precautions (5.1)].

7.4 All-Trans Retinoic Acid (Oral Tretinoin)

Tranexamic acid USP tablets are not recommended in patients with acute promyelocytic leukemia taking all-trans retinoic acid for remission induction because of possible exacerbation of the procoagulant effect of all-trans retinoic acid [see Warnings and Precautions (5.1)].

8 USE IN SPECIFIC POPULATIONS

8.1 Pregnancy

Risk Summary

Tranexamic acid USP tablets are not indicated for use in pregnant women. There is no available data on tranexamic acid USP tablets use in pregnant women to evaluate for a drug-associated risk of major birth defects, miscarriage or adverse maternal or fetal outcomes. Tranexamic acid crosses the placenta. Animal reproduction studies have not identified adverse developmental outcomes with oral administration of tranexamic acid to pregnant rats at doses up to 4 times the recommended human dose (see Data).

In the US general population, the estimated background risk of major birth defects and miscarriage in clinically recognized pregnancies is 2% to 4% and 15% to 20%, respectively.

Data

Animal Data

In a rat embryo-fetal developmental toxicity study, tranexamic acid had no adverse effects on embryo-fetal development when administered during the period of organogenesis (from gestation days 6 through 17) at twice daily doses of 0, 150, 375, and 750 mg/kg (1, 2 and 4 times the recommended human oral dosage of 3900 mg/day based on body surface area (mg/m^2)).

In a perinatal-postnatal developmental toxicity study in rats administered tranexamic acid from gestation day 6 through postnatal day 20 at twice daily doses of 0, 150, 375, and 750 mg/kg, no significant adverse effects on maternal behavior or body weight were observed, and no significant effects on pup viability, body weight, developmental milestones or adult fertility were observed. It was concluded that the no-observed-effect-level (NOEL) for this study was 1500 mg/kg/day in both F0 and F1 generations, which is equivalent to 4 times the recommended human oral dose of 3900 mg/day based on body surface area (mg/m^2).

8.2 Lactation

Risk Summary

Tranexamic acid is present in the mother’s milk at a concentration of about one hundredth of the corresponding serum concentration (see Data). The amount of tranexamic acid a nursing infant would absorb is unknown. There are no adequate data on the effects of tranexamic acid on the breastfed infant or the effects of tranexamic acid on milk production. The developmental and health benefits of breastfeeding should be considered along with the mother’s clinical need for tranexamic acid USP tablets and any potential adverse effects on the breast-fed child from tranexamic acid USP tablets or from the underlying maternal condition.

Data

Human Data

One hour after the last dose following a 2-day treatment course in lactating women, the milk concentration of the tranexamic acid was 1% of the peak serum concentration.

8.4 Pediatric Use

The safety and effectiveness of tranexamic acid USP tablets have been established in females of reproductive potential. Efficacy is expected to be the same for post-menarchal females under the age of 17 as for those 17 years and older. Tranexamic acid USP tablets are not indicated before menarche.

8.5 Geriatric Use

Tranexamic acid USP tablets are indicated for females of reproductive potential and is not intended for use by postmenopausal women.

8.6 Renal Impairment

The effect of renal impairment on the pharmacokinetics of tranexamic acid USP tablets has not been studied. Because tranexamic acid is primarily eliminated via the kidneys by glomerular filtration with more than 95% excreted as unchanged in urine, the recommended dosage in patient with renal impairment is lower than the recommended dosage in patients with normal renal function [see Dosage and Administration (2.2) and Clinical Pharmacology (12.3)].

8.7 Hepatic Impairment

The effect of hepatic impairment on the pharmacokinetics of tranexamic acid USP tablets has not been studied. Because only a small fraction of the drug is metabolized, the recommended dosage in patients with hepatic impairment is the same as in patients with normal hepatic function [see Clinical Pharmacology (12.3)].

10 OVERDOSAGE

There are no known cases of intentional overdose with tranexamic acid USP tablets and no subjects in the clinical program took more than 2 times the prescribed amount of tranexamic acid USP tablets in a 24-hour period (>7800 mg/day). However, cases of overdose of tranexamic acid have been reported. Based on these reports, symptoms of overdose may include gastrointestinal (nausea, vomiting, diarrhea); hypotensive (e.g., orthostatic symptoms); thromboembolic (arterial, venous, embolic); visual impairment; mental status changes; myoclonus; or rash. No specific information is available on the treatment of overdose with tranexamic acid USP tablets. In the event of overdose, employ the usual supportive measures (e.g., clinical monitoring and supportive therapy) as dictated by the patient’s clinical status.

11 DESCRIPTION

Tranexamic acid USP tablets is an antifibrinolytic drug administered orally. The chemical name is trans-4-aminomethyl-cyclohexanecarboxylic acid. The structural formula is:

Tranexamic acid is a white crystalline powder. It is freely soluble in water and in glacial acetic acid and is very slightly soluble in ethanol and practically insoluble in ether. The molecular formula is C8H15N02 and the molecular weight is 157.2.

Tranexamic acid USP tablets are provided as white oval-shaped tablets and are not scored. Each tablet is debossed with the marking “FP650.” The active ingredient in each tablet is 650 mg tranexamic acid. The inactive ingredients contained in each tablet are: microcrystalline cellulose, colloidal silicon dioxide, pregelatinized corn starch, povidone, hypromellose, stearic acid, and magnesium stearate.

12 CLINICAL PHARMACOLOGY

12.1 Mechanism of Action

Tranexamic acid is a synthetic lysine amino acid derivative, which diminishes the dissolution of hemostatic fibrin by plasmin. In the presence of tranexamic acid, the lysine receptor binding sites of plasmin for fibrin are occupied, preventing binding to fibrin monomers, thus preserving and stabilizing fibrin’s matrix structure.

The antifibrinolytic effects of tranexamic acid are mediated by reversible interactions at multiple binding sites within plasminogen. Native human plasminogen contains 4 to 5 lysine binding sites with low affinity for tranexamic acid (Kd = 750 μmol/L) and 1 with high affinity (Kd = 1.1 μmol/L). The high affinity lysine site of plasminogen is involved in its binding to fibrin. Saturation of the high affinity binding site with tranexamic acid displaces plasminogen from the surface of fibrin. Although plasmin may be formed by conformational changes in plasminogen, binding to and dissolution of the fibrin matrix is inhibited.

12.2 Pharmacodynamics

Tranexamic acid, at in vitro concentrations of 25 - 100 μM, reduces by 20 - 60% the maximal rate of plasmin lysis of fibrin catalyzed by tissue plasminogen activator (tPA).

Elevated concentrations of endometrial, uterine, and menstrual blood tPA are observed in women with heavy menstrual bleeding (HMB) compared to women with normal menstrual blood loss. The effect of tranexamic acid on lowering endometrial tPA activity and menstrual fluid fibrinolysis is observed in women with HMB receiving tranexamic acid total oral doses of 2-3 g/day for 5 days.

In healthy subjects, tranexamic acid at blood concentrations less than 10 mg/mL has no effect on the platelet count, the coagulation time or various coagulation factors in whole blood or citrated blood. Tranexamic acid, however, at blood concentrations of 1 and 10 mg/mL prolongs the thrombin time.

Cardiac Electrophysiology

The effect of tranexamic acid USP tablets on QT interval was evaluated in a randomized, single-dose, 4-way crossover study in 48 healthy females aged 18 to 49 years. Subjects received (1) tranexamic acid USP tablets 1300 mg (2) tranexamic acid USP tablets 3900 mg (three times the maximum recommended single dose), (3) moxifloxacin 400 mg, and (4) placebo. There was no significant increase in the corrected QT interval at any time up to 24 hours after the administration of either dose of tranexamic acid USP tablets. Moxifloxacin, the active control, was associated with a maximum 14.1 msec mean increase in corrected QT interval (moxifloxacin – placebo) at 3 hours after administration.

12.3 Pharmacokinetics

Absorption

After a single oral administration of 1300 mg of tranexamic acid USP tablets, the peak plasma concentration (Cmax) occurred at approximately 3 hours (Tmax). The absolute bioavailability of tranexamic acid USP tablets in women aged 18-49 is approximately 45%. Following multiple oral doses (1300 mg tablets three times daily) administration of tranexamic acid USP tablets for 5 days, the mean Cmax increased by approximately 19% and the mean area under the plasma concentration-time curve (AUC) remained unchanged, compared to a single oral dose administration (1300 mg). Plasma concentrations reached steady state at the 5th dose of tranexamic acid USP tablets on Day 2.

The mean plasma pharmacokinetic parameters of tranexamic acid determined in 19 healthy women following a single (1300 mg) and multiple (1300 mg tablets three times daily for 5 days) oral dose of tranexamic acid USP tablets are shown in Table 3.

Table 3. Mean (CV%) Pharmacokinetic Parameters Following a Single (1300 mg) and Multiple Dose (1300 mg three times daily for 5 days) Oral Administration of tranexamic acid USP tablets in 19 Healthy Women under Fasting Conditions
Parameter | Arithmetic Mean (CV%)
Parameter | Single dose | Multiple dose
Cmax (mcg/mL) | 13.83 (32.14) | 16.41 (26.19)
AUCtldc (mcg∙h/mL) | 77.96 (31.14) | 77.67a(29.39)
AUCinf (mcg∙h/mL) | 80.19 (30.43) | -
Tmax (h)b | 2.5 (1 – 5) | 2.5 (2 – 3.5)
t1/2 (h) | 11.08 (16.94) | -
Cmax = maximum concentration
AUCtldc = area under the drug concentration curve from time 0 to time of last determinable concentration
AUCinf = area under the drug concentration curve from time 0 to infinity
Tmax = time to maximum concentration
t1/2 = terminal elimination half-life
aAUC0-tau(mcg·h/mL) = area under the drug concentration curve from time 0 to 8 hours
bData presented as median (range)

Effect of food: Tranexamic acid USP tablets may be administered with or without food. A single dose administration (1300 mg) of tranexamic acid USP tablets with food increased both Cmax and AUC by 7% and 16%, respectively.

Distribution

Tranexamic acid is 3% bound to plasma proteins with no apparent binding to albumin. Tranexamic acid is distributed with an initial volume of distribution of 0.18 L/kg and steady-state apparent volume of distribution of 0.39 L/kg.

Tranexamic acid crosses the placenta. The concentration in cord blood after an intravenous injection of 10 mg/kg to pregnant women is about 30 mg/L, as high as in the maternal blood.

Tranexamic acid concentration in cerebrospinal fluid is about one tenth of the plasma concentration.

The drug passes into the aqueous humor of the eye achieving a concentration of approximately one tenth of plasma concentrations.

Elimination

Most elimination post intravenous administration occurred during the first 10 hours, giving an apparent elimination half-life of approximately 2 hours. The mean terminal half-life of tranexamic acid is approximately 11 hours. Plasma clearance of tranexamic acid is 110-116 mL/min.

Metabolism

A small fraction of the tranexamic acid is metabolized.

Excretion

Tranexamic acid is eliminated by urinary excretion primarily via glomerular filtration with more than 95% of the dose excreted unchanged. Excretion of tranexamic acid is about 90% at 24 hours after intravenous administration of 10 mg/kg.

Specific Populations

Pediatric Patients
Tranexamic acid USP tablets are indicated for females of reproductive age (not approved for use in premenarcheal girls).
In a randomized, single dose, two-way crossover study of two dose levels (650 mg and 1,300 mg), pharmacokinetics of tranexamic acid was evaluated in 20 female adolescents (12 to 16 years of age) with heavy menstrual bleeding. The Cmax and AUC values after a single oral dose of 650 mg in the adolescent females were 32 – 36% less than those after a single oral dose of 1,300 mg in the adolescent females. The Cmax and AUC values after a single oral dose of 1300 mg in the adolescent females were 20 – 25% less than those in the adult females given the same dose in a separate study. [See Use in Specific Populations (8.4)]

Patients with Renal Impairment
The effect of renal impairment on the disposition of tranexamic acid USP tablets has not been evaluated. Urinary excretion following a single intravenous injection of tranexamic acid declines as renal function decreases. Following a single 10 mg/kg intravenous injection of tranexamic acid in 28 patients, the 24-hour urinary fractions of tranexamic acid with serum creatinine concentrations 1.4 – 2.8, 2.8 – 5.7, and greater than 5.7 mg/dL were 51, 39, and 19%, respectively. The 24-hour tranexamic acid plasma concentrations for these patients demonstrated a direct relationship to the degree of renal impairment. Therefore, a lower dosage is needed in patients with renal impairment [see Dosage and Administration (2.2)].

Patients with Hepatic Impairment

The effect of hepatic impairment on the disposition of tranexamic acid USP tablets has not been evaluated. One percent and 0.5 percent of an oral dose are excreted as a dicarboxylic acid and acetylated metabolite, respectively. Because only a small fraction of the drug is metabolized, the recommended dosage in patients with hepatic impairment is the same as in patients with normal hepatic impairment.

Drug Interactions Studies

No drug-drug interaction studies were conducted with tranexamic acid USP tablets.

All-Trans Retinoic Acid (Oral Tretinoin)

In a study involving 28 patients with acute promyelocytic leukemia who were given either orally administered (1) all-trans retinoic acid plus intravenously administered tranexamic acid, (2) all-trans retinoic acid plus chemotherapy, or (3) all-trans retinoic acid plus tranexamic acid plus chemotherapy, all 4 patients who were given all-trans retinoic acid plus tranexamic acid died, with 3 of the 4 deaths due to thrombotic complications. The procoagulant effect of all-trans retinoic acid may have been exacerbated by concomitant use of tranexamic acid. Therefore, tranexamic acid USP tablets is not recommended in patients with acute promyelocytic leukemia taking all-trans retinoic acid [see Warnings and Precautions (5.1) and Drug Interactions (7.4)].

13 NONCLINICAL TOXICOLOGY

13.1 Carcinogenesis, Mutagenesis, Impairment of Fertility

Carcinogenesis

Carcinogenicity studies with tranexamic acid in male mice at doses as high as 6 times the recommended human dose of 3900 mg/day showed an increased incidence of leukemia which may have been related to treatment. Female mice were not included in this experiment.

The dose multiple referenced above is based on body surface area (mg/m^2). Actual daily dose in mice was up to 5000 mg/kg/day in food.

Hyperplasia of the biliary tract and cholangioma and adenocarcinoma of the intrahepatic biliary system have been reported in one strain of rats after dietary administration of doses exceeding the maximum tolerated dose for 22 months. Hyperplastic, but not neoplastic, lesions were reported at lower doses. Subsequent long-term dietary administration studies in a different strain of rat, each with an exposure level equal to the maximum level employed in the earlier experiment, have failed to show such hyperplastic/neoplastic changes in the liver.

Mutagenesis

Tranexamic acid was neither mutagenic nor clastogenic in the in vitro Bacterial Reverse Mutation Assay (Ames test), in vitro chromosome aberration test in Chinese hamster cells, and in in vivo chromosome aberration tests in mice and rats.

Impairment of Fertility

Reproductive studies performed in mice, rats and rabbits have not revealed any evidence of impaired fertility or adverse effects on the fetus due to tranexamic acid.

13.2 Animal Toxicology and/or Pharmacology

Ocular Effects

In a 9-month toxicology study, dogs were administered tranexamic acid in food at doses of 0, 200, 600, or 1200 mg/kg/day. These doses are approximately 2, 5, and 6 times, respectively, the recommended human oral dose of 3900 mg/day based on AUC. At 6 times the human dose, some dogs developed reversible reddening and gelatinous discharge from the eyes. Ophthalmologic examination revealed reversible changes in the nictitating membrane/conjunctiva. In some female dogs, the presence of inflammatory exudate over the bulbar conjunctival mucosa was observed. Histopathological examinations did not reveal any retinal alteration. No adverse effects were observed at 5 times the human dose.

In other studies, focal areas of retinal degeneration were observed in cats, dogs and rats following oral or intravenous tranexamic acid doses at 6-40 times the recommended usual human dose based on mg/m^2 (actual animal doses between 250-1600 mg/kg/day).

14 CLINICAL STUDIES

14.1 Overview of the Clinical Studies

The efficacy of tranexamic acid USP tablets in the treatment of heavy menstrual bleeding (HMB) in women of reproductive potential was demonstrated in two randomized, double-blind, placebo-controlled studies: one 3-cycle treatment study (Study 1) and one 6-cycle treatment study (Study 2) [see Adverse Reactions (6.1)]. In these studies, HMB was defined as an average menstrual blood loss of ≥ 80 mL as assessed by alkaline hematin analysis of collected sanitary products over two baseline menstrual cycles. Subjects were 18 to 49 years of age with a mean age of approximately 40 years, had cyclic menses every 21-35 days, and a BMI of approximately 32 kg/m2. On average, subjects had an HMB history of approximately 10 years and 40% had fibroids as determined by transvaginal ultrasound. Approximately 70% were Caucasian, 25% were Black, and 5% were Asian, Native American, Pacific Islander, or Other. Seven percent (7%) of all subjects were of Hispanic origin.

In these studies, the primary outcome measure was menstrual blood loss (MBL), measured using the alkaline hematin method. The endpoint was change from baseline in MBL, calculated by subtracting the mean MBL during treatment from the mean pretreatment MBL. The key secondary outcome measures were based on specific questions concerning limitations in social or leisure activities (LSLA) and limitations in physical activities (LPA). Large stains (soiling beyond the undergarment) were also included as a key secondary outcome measure.

14.2 Heavy Menstrual Bleeding in the Three-Cycle Treatment Study

Study 1 compared the effects of two doses of tranexamic acid USP tablets (1950 mg and 3900 mg per day for up to 5 days during each menstrual period) versus placebo on MBL over a 3-cycle treatment duration. Of the 294 evaluable subjects, 115 subjects received tranexamic acid USP tablets 1950 mg/day, 112 subjects received tranexamic acid USP tablets 3900 mg/day and 67 subjects received placebo (subjects took at least one dose of study drug and had post-treatment data available).

Results are shown in Table 4. Menstrual blood loss (MBL) was statistically significantly reduced in patients treated with 3900 mg/day tranexamic acid USP tablets compared to placebo. Study success also required achieving a reduction in MBL that was determined to be clinically meaningful to the subjects. The 1950 mg/day tranexamic acid USP tablets dose did not meet the criteria for success.

Tranexamic acid USP tablets also statistically significantly reduced limitations on social, leisure, and physical activities in the 3900 mg/day dose group compared to the placebo group (see Table 5). No statistically significant treatment difference was observed in response rates on the number of large stains.

14.3 Heavy Menstrual Bleeding in the Six-Cycle Treatment Study

Study 2 compared the effects of tranexamic acid USP tablets 3900 mg/day given daily for up to 5 days during each menstrual period versus placebo on menstrual blood loss (MBL) over a 6-cycle treatment duration. Of the 187 evaluable subjects, 115 subjects received tranexamic acid USP tablets and 72 subjects received placebo (subjects took at least one dose of study drug and had post-treatment data available).

Results are shown in Table 6. MBL was statistically significantly reduced in patients treated with 3900 mg/day tranexamic acid USP tablets compared to placebo. Study success also required achieving a reduction in MBL that was determined to be clinically meaningful to the subjects.

Table 6. Mean Reduction from Baseline in Menstrual Blood Loss in Women with Heavy Menstrual Bleeding (Study 2)
Treatment Arm | N | Baseline Mean MBL (mL) | Least Squares Mean Reduction in MBL (mL) | Percent Reduction in MBL
Tranexamic acid USP tablets 3900 mg/day | 115 | 172 | 66 [p<0.001 versus placebo] | 38%
Placebo | 72 | 153 | 18 | 12%

Limitations on social, leisure, and physical activities were also statistically significantly reduced in the tranexamic acid USP tablets group compared to placebo (see Table 7). No statistically significant treatment difference was observed in response rates on the number of large stains.

Table 7. Secondary Outcomes in 6-Cycle Study in Women with Heavy Menstrual Bleeding (Study 2)
Outcome Measure | N | Baseline Meana | Least Squares Mean Reductionb
Social and Leisure Activities
3900 mg/day tranexamic acid USP tablets | 115 | 2.92 | 0.85c
Placebo | 72 | 2.74 | 0.44
Physical Activities
3900 mg/day tranexamic acid USP tablets | 115 | 3.05 | 0.87c
Placebo | 72 | 2.90 | 0.40
 | N |  | Respondersd
Reduction in Large Stains
3900 mg/day tranexamic acid USP tablets | 115 |  | 57%e
Placebo | 72 |  | 51%
a Response categories: 1=not at all limited; 2=slightly limited; 3=moderately limited; 4=quite a bit limited; 5=extremely limited
b Positive means reflect an improvement from baseline
c p-value <0.05 versus placebo
d Responders are defined as subjects who experienced a reduction from baseline in frequency of large stains
e Non-significant difference versus placebo

14.4 Heavy Menstrual Bleeding Results over Time

The efficacy of tranexamic acid USP tablets 3900 mg/day over 3 menstrual cycles and over 6 menstrual cycles was demonstrated versus placebo in Studies 1 and 2 (see Figure 1). The change in menstrual bleeding loss from baseline was similar across all post-baseline treatment cycles.

Figure 1: Menstrual Bleeding Loss Levels over Duration of Therapy in Women with Heavy Menstrual Bleeding (Studies 1 and 2)

16 HOW SUPPLIED/STORAGE AND HANDLING

Tranexamic acid USP tablets are provided as white oval-shaped 650 mg tablets. Each tablet is debossed with the marking “FP650”and are supplied as:

NDC 50268-772-13 (10 tablets per card, 3 cards per carton).

STORAGE AND HANDLING

Dispensed in Unit Dose Package. For Institutional Use Only.

Storage

Store at room temperature 25° C (77° F); excursions permitted to 15-30° C (59-86° F). [See USP Controlled Room Temperature].

17 PATIENT COUNSELING INFORMATION

Advise the patient to read the FDA-approved patient labeling (Patient Information).

Thromboembolic Risk
Inform patients that tranexamic acid USP tablets may increase the risk of venous and arterial thrombosis or thromboembolism and to contact their healthcare provider for any signs or symptoms suggestive of thromboembolism [see Warnings and Precautions (5.1)].

Advise patients to discontinue use of tranexamic acid USP tablets and promptly report visual and ocular symptoms to their health care provider as retinal venous and arterial occlusion have been reported in patients using tranexamic acid USP tablets [see Warnings and Precautions (5.1)].

Severe Allergic Reactions
Inform patients that they should stop tranexamic acid USP tablets and seek immediate medical attention if they notice symptoms of a severe allergic reaction (e.g., shortness of breath or throat tightening) [see Warnings and Precautions (5.2)].

Administration Instructions
Instruct patients to take tranexamic acid USP tablets only during menstruation and for a maximum of 5 days each month [see Recommended Dosage (2.1)].

Manufactured for:
AvKARE
Pulaski, TN 38478

Mfg. Rev. 12/20
AV 09/22 (W)
AvPAK

PATIENT INFORMATION

TRANEXAMIC ACID (TRAN-ex-AM-ik AS-id), USP TABLETS, for oral use

Read the Patient Information that comes with tranexamic acid USP tablets before you start using the drug and each time you get a refill. There may be new information. This leaflet does not take the place of talking with your healthcare provider about your medical condition or your treatment.

What is tranexamic acid USP tablets?

Tranexamic acid USP tablets is a prescription medicine used to treat your heavy monthly period (menstruation) when your bleeding gets in the way of social, leisure and physical activities. Tranexamic acid USP tablets does not contain any hormones. On average, tranexamic acid USP tablets has been shown to lower the amount of blood lost during your monthly period by about one-third, but it is not meant to stop your period.

Tranexamic acid USP tablets is taken only during your period and is not meant to treat pre-menstrual symptoms (symptoms that occur before your bleeding starts). Tranexamic acid USP tablets does not affect your fertility and cannot be used as birth control. Tranexamic acid USP tablets does not protect you against diseases that you may get if you have unprotected sex.

Tranexamic acid USP tablets has not been studied in adolescents younger than 18 years of age.

Tranexamic acid is not for women who have already gone through menopause (post-menopausal).

Who should not take tranexamic acid USP tablets?

Do not take tranexamic acid USP tablets if you:

- Are using a form of birth control that contains estrogen and a progestin (like a birth control pill, patch, or vaginal ring). Ask your healthcare provider before taking tranexamic acid USP tablets if you are not sure if your birth control method contains estrogen and a progestin.
- Currently have a blood clot
- Have ever had a blood clot
- Have been told that you are at risk of having a blood clot
- Are allergic to tranexamic acid

What should I tell my healthcare provider before taking tranexamic acid USP tablets?

Before taking tranexamic acid USP tablets, tell your healthcare provider about all of your medical conditions, including whether:

- You have ever had a blood clot or been told that you are at risk of having a blood clot
- You are using a form of birth control that contains estrogen and a progestin (like a birth control pill, patch, or vaginal ring). Using hormonal birth control along with tranexamic acid USP tablets may increase your chance of having a serious blood clot, stroke, or heart attack. For this reason, do not use tranexamic acid USP tablets if you use a form of birth control that contains estrogen and a progestin.
- You are pregnant or think you may be pregnant
- You are breastfeeding or plan to breast-feed. Tranexamic acid USP tablets can pass into your milk. Talk to your healthcare provider about the best way to feed your baby if you take tranexamic acid USP tablets.
- The time between the start of your periods is less than 21 days or more than 35 days
- You have any other medical conditions

Tell your healthcare provider about all the medicines you take, including prescription and over-the-counter medicines, vitamins, and herbal supplements. Tranexamic acid USP tablets and other medicines can affect each other, causing side effects. Tranexamic acid USP tablets can affect the way other medicines work and other medicines can affect how tranexamic acid USP tablets works.

Especially tell your healthcare provider if you take:

- Birth control pills or other hormonal birth control
- Medicines used to help your blood form clots
- Medicines used to break up blood clots
- Any medicines to treat leukemia

Ask your healthcare provider if you are not sure if your medicine is one that is described above.

How should I take tranexamic acid USP tablets?

- Take tranexamic acid USP tablets exactly as your healthcare provider tells you.
- Do not take tranexamic acid USP tablets until your period has started.
- Do not take tranexamic acid USP tablets for more than 5 days in a row.
- Do not take tranexamic acid USP tablets when you do not have your period.
- Once your period has started, take 2 tablets of tranexamic acid USP tablets three times per day (e.g., in the morning, afternoon, and evening).
- Tranexamic acid USP tablets should be swallowed whole and not chewed or broken apart.
- Tranexamic acid USP tablets may be taken with or without food.
- Do not take more than 6 tablets of tranexamic acid USP tablets in a day. If you take more than 6 tablets, call your healthcare provider.
- If you miss a dose, take it when you remember, and then take your next dose at least six hours later. Do not take more than two tablets at a time to make up for missed doses.
- If tranexamic acid USP tablets does not help to lessen bleeding with your periods after 2 cycles or seems to stop working, talk to your healthcare provider.

What are the possible side effects of tranexamic acid USP tablets?

Tranexamic acid USP tablets can cause serious side effects, including:

- Blood clots. You may have a higher risk of having serious blood clots if you take tranexamic acid USP tablets with:
  - medicines used to help your blood form clots
  - some medicines used to treat leukemia
- Eye changes. Stop taking tranexamic acid USP tablets and promptly report any eye problems you have while taking tranexamic acid USP tablets. Your doctor will refer you to an eye doctor who will examine your eyes.
- Allergic reaction. If you have severe shortness of breath and your throat feels tight, stop taking tranexamic acid USP tablets and get medical care right away.

The most common side effects of tranexamic acid USP tablets include:

- Headaches
- Sinus and nasal problems
- Back pain
- Pain in your abdomen
- Pain in your muscles or joints
- Anemia
- Fatigue

Tell your healthcare provider if you have any side effect that bothers you or does not go away.

These are not all of the possible side effects of tranexamic acid USP tablets. For more information, ask your healthcare provider or pharmacist.

If you notice a change in your usual bleeding pattern that worries you, or your heavy bleeding continues, contact your healthcare provider right away. This may be a sign of a more serious condition.

Call your healthcare provider for medical advice about side effects. You may report side effects to the FDA at 1-800-FDA-1088. You may also report side effects to Amring Pharmaceuticals Inc. at 1-844-Amring1 (1-844-267-4641).

How should I store tranexamic acid USP tablets?

Store tranexamic acid USP tablets at room temperature between 59°F to 86°F (15°C to 30°C).

Keep tranexamic acid USP tablets and all medicines out of the reach of children.

General information about tranexamic acid USP tablets

Medicines are sometimes prescribed for conditions that are not mentioned in Patient Information Leaflets. Do not use tranexamic acid USP tablets for a condition for which it was not prescribed. Do not give tranexamic acid USP tablets to other people, even if they have the same symptoms that you have. It may harm them.

This patient information leaflet summarizes the most important information about tranexamic acid USP tablets. If you would like more information about tranexamic acid USP tablets, talk with your healthcare provider. You can ask your healthcare provider or pharmacist for information about tranexamic acid USP tablets that is written for healthcare professionals. For more information, call AvKARE at 1-855-361-3993.

What are the ingredients of tranexamic acid USP tablets?

Active ingredient: tranexamic acid

Inactive ingredients: microcrystalline cellulose, colloidal silicon dioxide, pregelatinized corn starch, povidone, hypromellose, stearic acid, and magnesium stearate.

This Patient Information has been approved by the U.S. Food and Drug Administration.

Manufactured for:
AvKARE
Pulaski, TN 38478

Mfg. Rev. 12/20
AV 09/22 (W)
AvPAK